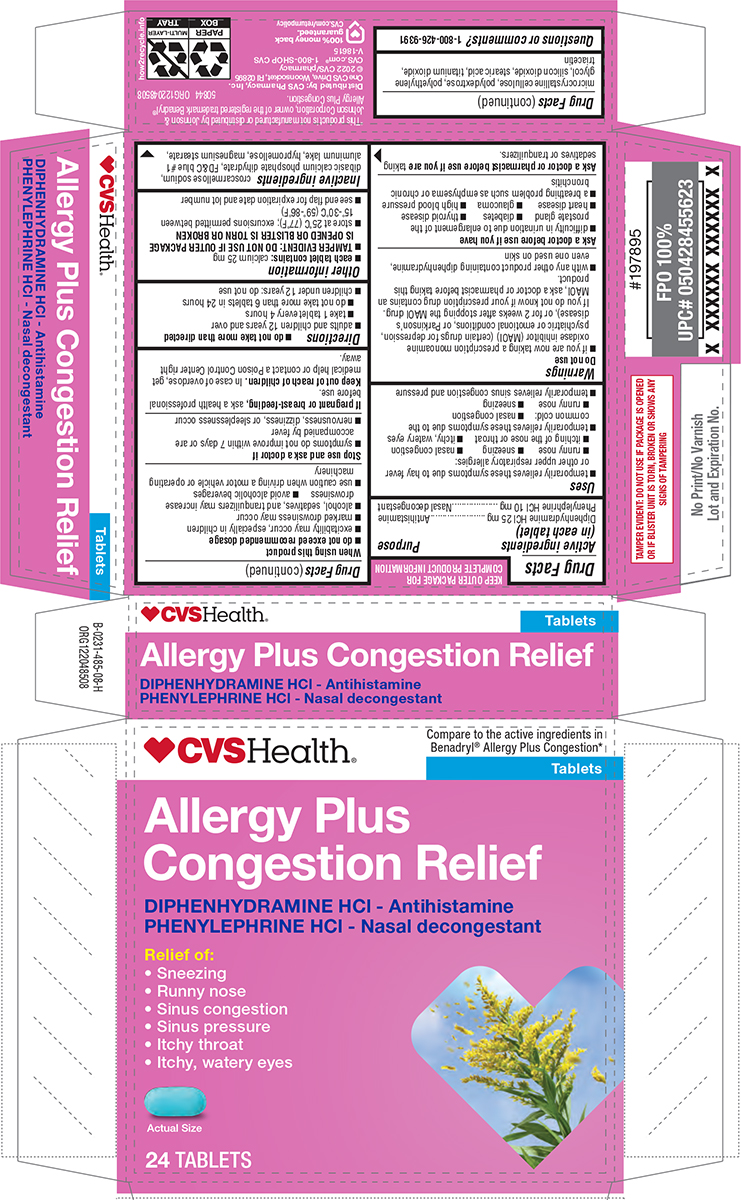 DRUG LABEL: Allergy Plus Congestion Relief
NDC: 51316-485 | Form: TABLET, FILM COATED
Manufacturer: CVS WOONSOCKET PRESCRIPTION CENTER, INCORPORATED
Category: otc | Type: HUMAN OTC DRUG LABEL
Date: 20260211

ACTIVE INGREDIENTS: DIPHENHYDRAMINE HYDROCHLORIDE 25 mg/1 1; PHENYLEPHRINE HYDROCHLORIDE 10 mg/1 1
INACTIVE INGREDIENTS: CROSCARMELLOSE SODIUM; DIBASIC CALCIUM PHOSPHATE DIHYDRATE; FD&C BLUE NO. 1 ALUMINUM LAKE; HYPROMELLOSE, UNSPECIFIED; MAGNESIUM STEARATE; MICROCRYSTALLINE CELLULOSE; POLYDEXTROSE; POLYETHYLENE GLYCOL, UNSPECIFIED; SILICON DIOXIDE; STEARIC ACID; TITANIUM DIOXIDE; TRIACETIN

CVS 44-485 Allergy Plus

Active ingredients (in each tablet)

Diphenhydramine HCl 25 mg
Phenylephrine HCl 10 mg

Purpose

Antihistamine
Nasal decongestant

Uses

- temporarily relieves these symptoms due to hay fever or other upper respiratory allergies:
  - runny nose
  - sneezing
  - nasal congestion
  - itching of the nose or throat
  - itchy, watery eyes
- temporarily relieves these symptoms due to the common cold:
  - nasal congestion
  - runny nose
  - sneezing
- temporarily relieves sinus congestion and pressure

Warnings

Do not use

- if you are now taking a prescription monoamine oxidase inhibitor (MAOI) (certain drugs for depression, psychiatric or emotional conditions, or Parkinson’s disease), or for 2 weeks after stopping the MAOI drug. If you do not know if your prescription drug contains an MAOI, ask a doctor or pharmacist before taking this product.
- with any other product containing diphenhydramine, even one used on skin

Ask a doctor before use if you have

- difficulty in urination due to enlargement of the prostate gland
- diabetes
- thyroid disease
- heart disease
- glaucoma
- high blood pressure
- a breathing problem such as emphysema or chronic bronchitis

Ask a doctor or pharmacist before use if you are

taking sedatives or tranquilizers.

When using this product

- do not exceed recommended dosage
- excitability may occur, especially in children
- marked drowsiness may occur
- alcohol, sedatives, and tranquilizers may increase drowsiness
- avoid alcoholic beverages
- use caution when driving a motor vehicle or operating machinery

Stop use and ask a doctor if

- symptoms do not improve within 7 days or are accompanied by fever
- nervousness, dizziness, or sleeplessness occur

If pregnant or breast-feeding,

ask a health professional before use.

Keep out of reach of children.

In case of overdose, get medical help or contact a Poison Control Center right away.

Directions

- do not take more than directed
- adults and children 12 years and over
  - take 1 tablet every 4 hours
  - do not take more than 6 tablets in 24 hours
- children under 12 years: do not use

Other information

- each tablet contains: calcium 25 mg
- TAMPER EVIDENT: DO NOT USE IF OUTER PACKAGE IS OPENED OR BLISTER IS TORN OR BROKEN
- store at 25°C (77°F); excursions permitted between 15°-30°C (59°-86°F)
- see end flap for expiration date and lot number

Inactive ingredients

croscarmellose sodium, dibasic calcium phosphate dihydrate, FD&C blue #1 aluminum lake, hypromellose, magnesium stearate, microcrystalline cellulose, polydextrose, polyethylene glycol, silicon dioxide, stearic acid, titanium dioxide, triacetin

Questions or comments?

1-800-426-9391

Principal display panel

♥CVSHealth®

Compare to the active ingredients in
Benadryl® Allergy Plus Congestion*
Tablets

Allergy Plus
Congestion Relief

DIPHENHYDRAMINE HCl - Antihistamine
PHENYLEPHRINE HCl - Nasal decongestant

Relief of:

- Sneezing
- Runny nose
- Sinus congestion
- Sinus pressure
- Itchy throat
- Itchy, watery eyes

Actual Size

24 TABLETS

TAMPER EVIDENT: DO NOT USE IF PACKAGE IS OPENED #197895
OR IF BLISTER UNIT IS TORN, BROKEN OR SHOWS ANY
SIGNS OF TAMPERING

*This product is not manufactured or distributed by Johnson &
Johnson Corporation, owner of the registered trademark Benadryl®
Allergy Plus Congestion.
Distributed by: CVS Pharmacy, Inc.
One CVS Drive, Woonsocket, RI 02895
© 2022 CVS/pharmacy
CVS.com® 1-800-SHOP CVS
V-18615
CVS.com/returnpolicy
100% money back
guaranteed.
50844 ORG122048508

CVS 44-485